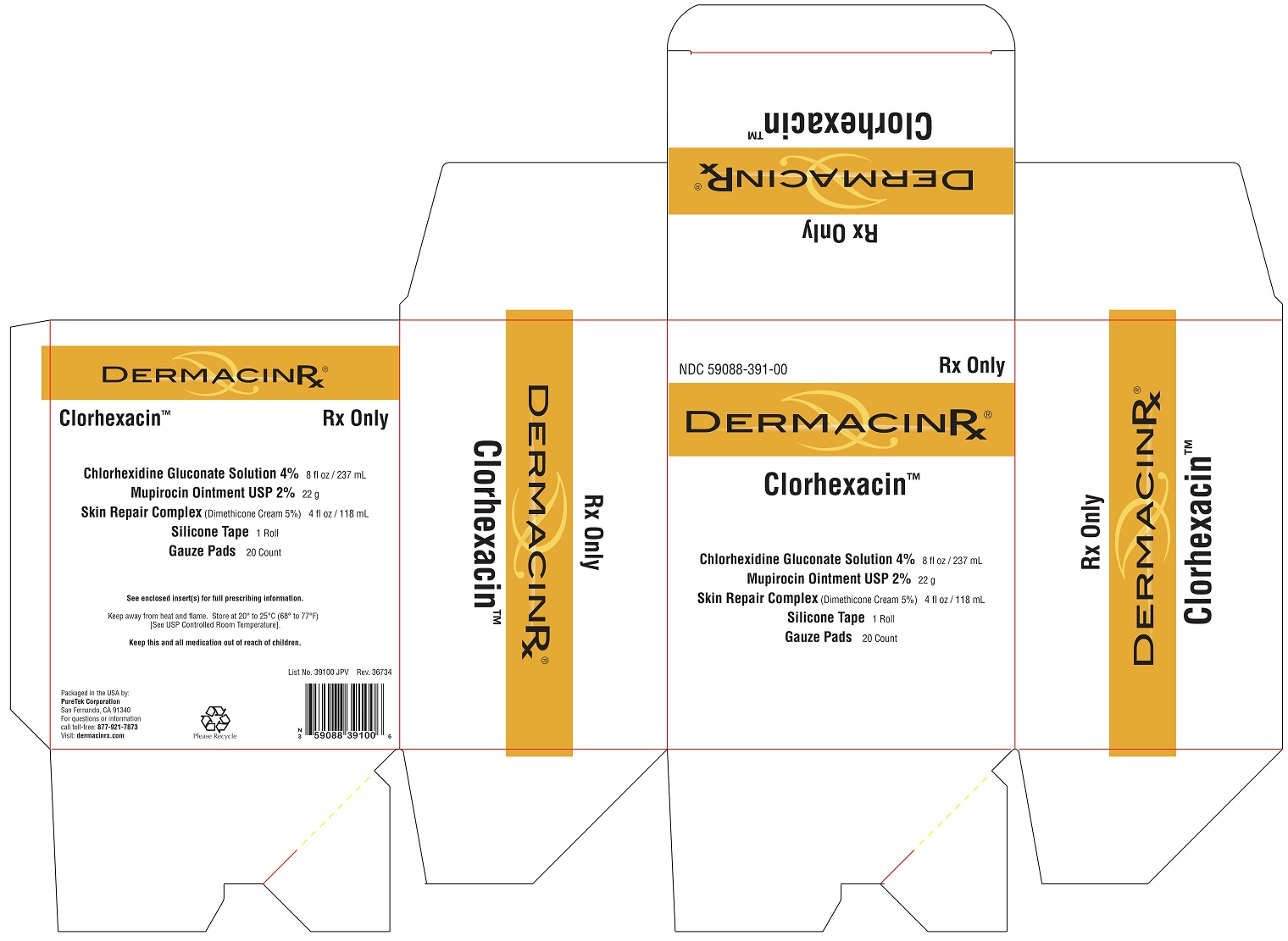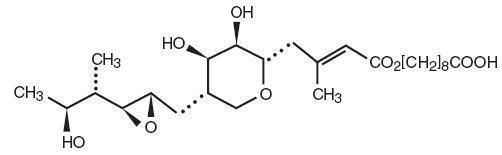 DRUG LABEL: DermacinRx Clorhexacin
NDC: 59088-391 | Form: KIT | Route: TOPICAL
Manufacturer: PureTek Corporation
Category: prescription | Type: HUMAN PRESCRIPTION DRUG LABEL
Date: 20241213

ACTIVE INGREDIENTS: MUPIROCIN 20 mg/1 g; CHLORHEXIDINE GLUCONATE 4 g/100 mL; DIMETHICONE 50 mg/1 mL
INACTIVE INGREDIENTS: POLYETHYLENE GLYCOL, UNSPECIFIED; COCO DIETHANOLAMIDE; HYDROXYETHYL CELLULOSE (2000 CPS AT 1%); ISOPROPYL ALCOHOL; LAURAMINE OXIDE; WATER; TRIDECYL ALCOHOL; GLUCONOLACTONE; PEG-75 LANOLIN; KUKUI NUT OIL; ALOE VERA LEAF; BUTYLENE GLYCOL; CAPRYLYL GLYCOL; SAFFLOWER OIL; CETYL ALCOHOL; CHLORPHENESIN; DIMETHICONE/DIENE DIMETHICONE CROSSPOLYMER; EDETATE DISODIUM; GLYCERIN; GLYCERYL MONOSTEARATE; LEVOMENOL; CALCIUM PANTOTHENATE; CARTHAMUS TINCTORIUS SEED OLEOSOMES; MALTODEXTRIN; NIACINAMIDE; PYRIDOXINE HYDROCHLORIDE; SILICON DIOXIDE; SODIUM ASCORBYL PHOSPHATE; .ALPHA.-TOCOPHEROL ACETATE, DL-; GINGER; PEG-100 STEARATE; PENTAERYTHRITOL TETRAKIS(3-(3,5-DI-TERT-BUTYL-4-HYDROXYPHENYL)PROPIONATE); PHENOXYETHANOL; WATER; HYALURONATE SODIUM; STEARIC ACID; TROLAMINE

DermacinRx Clorhexacin

Mupirocin Ointment USP, 2%

For Dermatologic Use

Rx Only

DESCRIPTION

Each gram of Mupirocin Ointment USP, 2% contains 20 mg mupirocin in a bland water miscible ointment base (polyethylene glycol ointment, NF) consisting of polyethylene glycol 400 and polyethylene glycol 3350. Mupirocin is a naturally occurring antibiotic. The chemical name is (E)-(2 S,3 R,4 R,5 S)-5-[(2 S,3 S,4 S,5 S)-2,3-Epoxy-5-hydroxy-4-methylhexyl]tetrahydro-3,4-dihydroxy-β-methyl-2H-pyran-2-crotonic acid, ester with 9-hydroxynonanoic acid. The molecular formula of mupirocin is C26H44O9 and the molecular weight is 500.62. The chemical structure is:

CLINICAL PHARMACOLOGY

Application of^14C-labeled mupirocin ointment to the lower arm of normal male subjects followed by occlusion for 24 hours showed no measurable systemic absorption (<1.1 nanogram mupirocin per milliliter of whole blood). Measurable radioactivity was present in the stratum corneum of these subjects 72 hours after application.

Following intravenous or oral administration, mupirocin is rapidly metabolized. The principal metabolite, monic acid, is eliminated by renal excretion, and demonstrates no antibacterial activity. In a study conducted in 7 healthy adult male subjects, the elimination half-life after intravenous administration of mupirocin was 20 to 40 minutes for mupirocin and 30 to 80 minutes for monic acid. The pharmacokinetics of mupirocin has not been studied in individuals with renal insufficiency.

Microbiology -
Mupirocin is an antibacterial agent produced by fermentation using the organism Pseudomonas fluorescens. It is active against a wide range of gram-positive bacteria including methicillin-resistant Staphylococcus aureus (MRSA). It is also active against certain gram-negative bacteria. Mupirocin inhibits bacterial protein synthesis by reversibly and specifically binding to bacterial isoleucyl transfer-RNA synthetase. Due to this unique mode of action, mupirocin demonstrates no in vitro cross-resistance with other classes of antimicrobial agents.

Resistance occurs rarely. However, when mupirocin resistance does occur, it appears to result from the production of a modified isoleucyl-tRNA synthetase. High-level plasmid-mediated resistance (MIC > 1024 mcg/mL) has been reported in some strains of S. aureus and coagulase-negative staphylococci.

Mupirocin is bactericidal at concentrations achieved by topical administration. However, the minimum bactericidal concentration (MBC) against relevant pathogens is generally 8-fold to 30-fold higher than the minimum inhibitory concentration (MIC). In addition, mupirocin is highly protein bound (>97%), and the effect of wound secretions on the MICs of mupirocin has not been determined.

Mupirocin has been shown to be active against most strains of S. aureus and Streptococcus pyogenes, both in vitro and in clinical studies (see INDICATIONS AND USAGE). The following in vitro data are available, BUT THEIR CLINICAL SIGNIFICANCE IS UNKNOWN. Mupirocin is active against most strains of Staphylococcus epidermidis and Staphylococcus saprophyticus.

INDICATIONS AND USAGE

Mupirocin Ointment USP, 2% is indicated for the topical treatment of impetigo due to: S. aureus and S. pyogenes.

CONTRAINDICATIONS

This drug is contraindicated in individuals with a history of sensitivity reactions to any of its components.

WARNINGS

Mupirocin Ointment USP, 2% is not for ophthalmic use.

PRECAUTIONS

If a reaction suggesting sensitivity or chemical irritation should occur with the use of Mupirocin Ointment USP, 2%, treatment should be discontinued and appropriate alternative therapy for the infection instituted.

As with other antibacterial products, prolonged use may result in overgrowth of nonsusceptible organisms, including fungi.

Mupirocin Ointment USP, 2% is not formulated for use on mucosal surfaces. Intranasal use has been associated with isolated reports of stinging and drying. A paraffin-based formulation - *Bactroban Nasal® (mupirocin calcium ointment) – is available for intranasal use.

Polyethylene glycol can be absorbed from open wounds and damaged skin and is excreted by the kidneys. In common with other polyethylene glycol-based ointments, Mupirocin Ointment USP, 2% should not be used in conditions where absorption of large quantities of polyethylene glycol is possible, especially if there is evidence of moderate or severe renal impairment.

Information for Patients -
Use this medication only as directed by your healthcare provider. It is for external use only. Avoid contact with the eyes. The medication should be stopped and your healthcare practitioner contacted if irritation, severe itching, or rash occurs. If impetigo has not improved in 3 to 5 days, contact your healthcare practitioner.

Drug Interactions -
The effect of the concurrent application of Mupirocin Ointment USP, 2% and other drug products has not been studied.

Carcinogenesis, Mutagenesis, Impairment of Fertility -
Long-term studies in animals to evaluate carcinogenic potential of mupirocin have not been conducted.

Results of the following studies performed with mupirocin calcium or mupirocin sodium in vitro and in vivo did not indicate a potential for genotoxicity: Rat primary hepatocyte unscheduled DNA synthesis, sediment analysis for DNA strand breaks, Salmonella reversion test (Ames), Escherichia coli mutation assay, metaphase analysis of human lymphocytes, mouse lymphoma assay, and bone marrow micronuclei assay in mice.

Reproduction studies were performed in male and female rats with mupirocin administered subcutaneously at doses up to 14 times a human topical dose (approximately 60 mg mupirocin per day) on a mg/m^2 basis and revealed no evidence of impaired fertility and reproductive performance from mupirocin.

Pregnancy:
Teratogenic Effects -
Reproduction studies have been performed in rats and rabbits with mupirocin administered subcutaneously at doses up to 22 and 43 times, respectively, the human topical dose (approximately 60 mg mupirocin per day) on a mg/m^2 basis and revealed no evidence of harm to the fetus due to mupirocin. There are however, no adequate and well-controlled studies in pregnant women. Because animal studies are not always predictive of human response, this drug should be used during pregnancy only if clearly needed.

Nursing Mothers -
It is not known whether this drug is excreted in human milk. Because many drugs are excreted in human milk, caution should be exercised when Mupirocin Ointment USP, 2% is administered to a nursing woman.

Pediatric Use -
The safety and effectiveness of Mupirocin Ointment USP, 2% have been established in the age range of 2 months to 16 years. Use of mupirocin ointment USP, 2% in these age groups is supported by evidence from adequate and well-controlled studies of mupirocin ointment USP, 2% in impetigo in pediatric patients studied as part of the pivotal clinical trials (see CLINICAL STUDIES).

ADVERSE REACTIONS

The following local adverse reactions have been reported in connection with the use of mupirocin ointment USP, 2%: Burning, stinging, or pain in 1.5% of patients; itching in 1% of patients; rash, nausea, erythema, dry skin, tenderness, swelling, contact dermatitis, and increased exudate in less than 1% of patients. Systemic reactions to mupirocin ointment USP, 2% have occurred rarely.

DOSAGE AND ADMINISTRATION

A small amount of Mupirocin Ointment USP, 2% should be applied to the affected area 3 times daily. The area treated may be covered with a gauze dressing if desired. Patients not showing a clinical response within 3 to 5 days should be re-evaluated.

CLINICAL STUDIES

The efficacy of topical mupirocin ointment USP, 2% in impetigo was tested in two studies. In the first, patients with impetigo were randomized to receive either mupirocin ointment USP, 2% or vehicle placebo three times daily for 8 to 12 days. Clinical efficacy rates at end of therapy in the evaluable populations (adults and pediatric patients included) were 71% for mupirocin ointment USP, 2% (n=49) and 35% for vehicle placebo (n=51). Pathogen eradication rates in the evaluable populations were 94% for mupirocin ointment USP, 2% and 62% for vehicle placebo. There were no side effects reported in the group receiving mupirocin ointment USP, 2%.

In the second study, patients with impetigo were randomized to receive either mupirocin ointment USP, 2% three times daily or 30 to 40 mg/kg oral erythromycin ethylsuccinate per day (this was an unblinded study) for 8 days. There was a follow-up visit 1 week after treatment ended. Clinical efficacy rates at the follow-up visit in the evaluable populations (adults and pediatric patients included) were 93% for mupirocin ointment USP, 2% (n=29) and 78.5% for erythromycin (n=28). Pathogen eradication rates in the evaluable patient populations were 100% for both test groups. There were no side effects reported in the group receiving mupirocin ointment.

Pediatrics -
There were 91 pediatric patients aged 2 months to 15 years in the first study described above. Clinical efficacy rates at end of therapy in the evaluable populations were 78% for mupirocin ointment USP, 2% (n=42) and 36% for vehicle placebo (n=49). In the second study described above, all patients were pediatric except two adults in the group receiving mupirocin ointment USP, 2%. The age range of the pediatric patients was 7 months to 13 years. The clinical efficacy rate for mupirocin ointment USP, 2% (n=27) was 96%, and for erythromycin it was unchanged (78.5%).

HOW SUPPLIED

Mupirocin Ointment USP, 2% is available as follows:
22 gram tube (NDC 45802-112-22)

Store at 20-25°C (68-77°F) [see USP Controlled Room Temperature].

*Bactroban Nasal® is a registered trademark of GlaxoSmithKline.

Chlorhexidine Gluconate Solution, 4%

Drug Facts

Active ingredient

Chlorhexidine Gluconate 4% solution

Purpose

Antiseptic

Uses

- surgical hand scrub: significantly reduces the number of microorganisms on the hands and forearms prior to surgery or patient care
- healthcare personnel handwash: helps reduce bacteria that potentially can cause disease
- patient preoperative skin preparation: for the preparation of the patient's skin prior to surgeryskin wound and general skin cleansing
- skin wound and general skin cleansing

Warnings

For external use only.

Do not use

- if you are allergic to chlorhexidine gluconate or any other ingredients
- in contact with meninges
- in the genital area
- as a preoperative skin preparation of the head or face

When using this product

- keep out of eyes, ears, and mouth. May cause serious and permanent eye injury if placed or kept in the eye during surgical procedures or may cause deafness when instilled in the middle ear through perforated eardrums.
- if solution should contact these areas, rinse out promptly and thoroughly with water
- wounds which involve more than the superficial layers of the skin should not be routinely treated
- repeated general skin cleansing of large body areas should not be done except when the underlying condition makes it necessary to reduce the bacterial population of skin

Stop use and ask a doctor
if irritation, sensitization or allergic reaction occurs. These may be signs of a serious condition.

Keep out of reach of children
if swallowed, get medical help or contact a Poison Control Center right away.

Directions

- use with care in premature infants and infants under 2 months of age. These products may cause irritation or chemical burns.

Surgical hand scrub:

- wet hands and forearms with water
- scrub for 3 minutes with about 5 ml of product and a wet brush paying close attention to the nails, cuticles and interdigital spaces
- a separate nail cleaner may be used
- rinse thoroughly
- wash for an additional 3 minutes with 5 ml of product and rinse under running water
- dry thoroughly

Healthcare personnel handwash:

- wet hands with water
- dispense about 5 ml of product into cupped hands and wash in a vigorous manner for 15 seconds
- rinse and dry thoroughly

Patient preoperative skin preparation:

- apply product liberally to surgical site and swab for at least 2 minutes and dry with a sterile towel
- repeat procedure for an additional 2 minutes and dry with a sterile towel

Skin wound and general skin cleaning:

- thoroughly rinse the area to be cleaned with water
- apply the minimum amount of product necessary to cover the skin or wound area and wash gently
- rinse again thoroughly

Other information

- store at 20-25ºC (68-77ºF)
- avoid excessive heat above 40ºC (104ºF)

Inactive ingredients

cocamide DEA, fragrance, glucono-delta-lactone, hydroxyethylcellulose, isopropyl alcohol, lauramine oxide, PEG-75 lanolin, purified water, tridecyl alcohol.

DermacinRx Skin Repair Complex (Dimethicone 5.0%)

Drug Facts

Active ingredient

Dimethicone 5.0%

Purpose

Skin Protectant

Uses

- for the treatment and/or prevention of diaper rash
- temporarily protects and helps relieve chapped or cracked skin

Warnings

For external use only

Do not use on

- deep or puncture wounds
- animal bites
- serious burns

When using this product

- do not get into eyes

Stop use and ask a doctor if

- condition worsens
- symptoms last more than 7 days or clear up and occur again within a few days

Keep out of reach of children. If swallowed, get medical help or contact a Poison Control Center right away.

Directions

- apply cream liberally as needed

Other information

- protect from freezing
- avoid excessive heat

Inactive ingredients

Aleurites moluccana seed oil, Aloe barbadensis (Aloe vera) leaf juice, butylene glycol, caprylyl glycol, Carthamus tinctorius (safflower) seed oil, cetyl alcohol, chlorphenesin, dimethicone crosspolymer, disodium EDTA, fragrance, glycerin, glyceryl stearate, DermacinRx Complex® [consisting of: bisabolol, calcium pantothenate (vitamin B5), Carthamus tinctorius (safflower) oleosomes, maltodextrin, niacinamide (vitamin B3), pyridoxine HCl (vitamin B6), silica, sodium ascorbyl phosphate (vitamin C), sodium starch octenylsuccinate, tocopheryl acetate (vitamin E), Zingiber officinale (ginger) root extract], PEG-100 stearate, pentaerythrityl tetra-di-t-butyl hydroxyhydrocinnamate, phenoxyethanol, purified water, sodium hyaluronate, stearic acid, triethanolamine.

Silicone Tape

Uses
• To be applied to wounds or scars as a protective silicone barrier.
• As a dressing for abrasions, surgical wounds, donor sites, lacerations, ulcers, skin tears, superficial partial thickness burns, venous leg ulcers.
• As a dressing/securement for IV related uses, pressure ulcers, skin care, and wound care

Precautions
• Do not use if you are allergic to silicone
• Keep out of reach of children

Directions for use
• Apply tape to wound or scar as needed or as directed by your physician. Remove tape, wash area, and apply new tape at least every 24 hours.